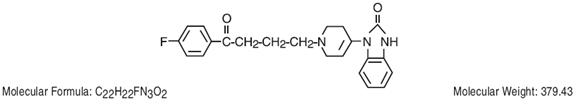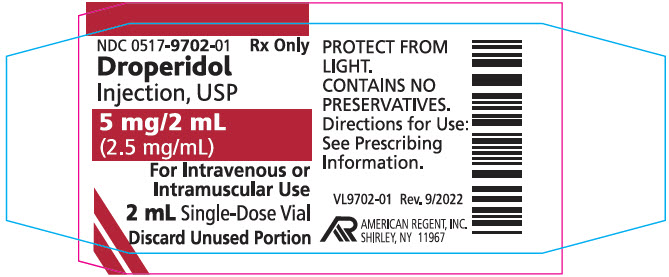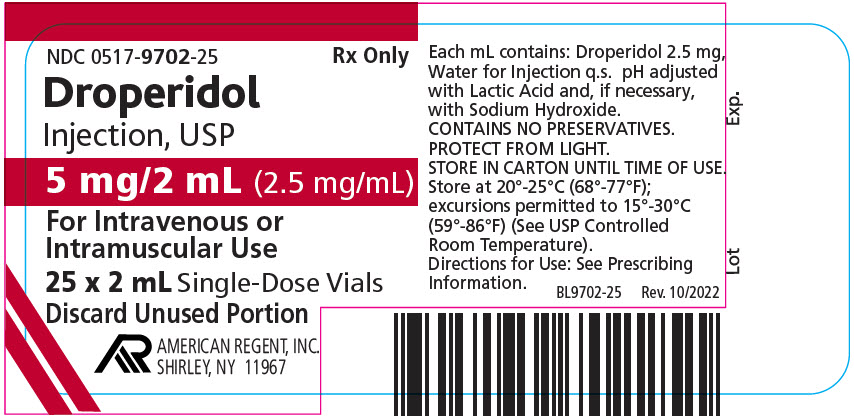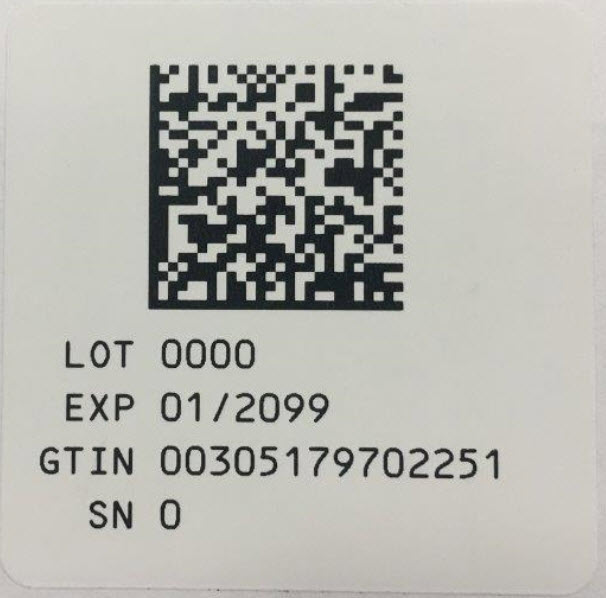 DRUG LABEL: Droperidol
NDC: 0517-9702 | Form: INJECTION, SOLUTION
Manufacturer: American Regent, Inc.
Category: prescription | Type: HUMAN PRESCRIPTION DRUG LABEL
Date: 20230320

ACTIVE INGREDIENTS: DROPERIDOL 2.5 mg/1 mL
INACTIVE INGREDIENTS: LACTIC ACID; SODIUM HYDROXIDE; WATER

DROPERIDOL INJECTION, USP

For IV or IM Use Only

Rx Only

WARNING

Cases of QT prolongation and/or torsade de pointes have been reported in patients receiving droperidol at doses at or below recommended doses. Some cases have occurred in patients with no known risk factors for QT prolongation and some cases have been fatal.

Due to its potential for serious proarrhythmic effects and death, droperidol should be reserved for use in the treatment of patients who fail to show an acceptable response to other adequate treatments, either because of insufficient effectiveness or the inability to achieve an effective dose due to intolerable adverse effects from those drugs (see CONTRAINDICATIONS, WARNINGS, PRECAUTIONS, and ADVERSE REACTIONS).

Cases of QT prolongation and serious arrhythmias (e.g., torsade de pointes) have been reported in patients treated with droperidol. Based on these reports, all patients should undergo a 12-lead ECG prior to administration of droperidol to determine if a prolonged QT interval (i.e., QTc greater than 440 msec for males or 450 msec for females) is present. If there is a prolonged QT interval, droperidol should NOT be administered. For patients in whom the potential benefit of droperidol treatment is felt to outweigh the risks of potentially serious arrhythmias, ECG monitoring should be performed prior to treatment and continued for 2-3 hours after completing treatment to monitor for arrhythmias.

Droperidol is contraindicated in patients with known or suspected QT prolongation, including patients with congenital long QT syndrome.

Droperidol should be administered with extreme caution to patients who may be at risk for development of prolonged QT syndrome (e.g., congestive heart failure, bradycardia, use of a diuretic, cardiac hypertrophy, hypokalemia, hypomagnesemia, or administration of other drugs known to increase the QT interval). Other risk factors may include age over 65 years, alcohol abuse, and use of agents such as benzodiazepines, volatile anesthetics, and IV opiates. Droperidol should be initiated at a low dose and adjusted upward, with caution, as needed to achieve the desired effect.

DESCRIPTION

Droperidol Injection, USP, is a sterile, non-pyrogenic, aqueous solution for intravenous or intramuscular use only.

Each mL contains:

Droperidol…………………………………….2.5 mg

Water for Injection………………………........q.s.

pH adjusted between 3.0 and 3.8 with lactic acid and, if necessary, with sodium hydroxide.

Droperidol is a neuroleptic (tranquilizer) agent. Chemically it is 1-(1-[3-(p-fluorobenzoyl)propyl]-1,2,3,6-tetrahydro-4-pyridyl)-2-benzimidazolinone and the structural formula is:

CLINICAL PHARMACOLOGY

Droperidol produces marked tranquilization and sedation. It allays apprehension and provides a state of mental detachment and indifference while maintaining a state of reflex alertness.

Droperidol produces an antiemetic effect as evidenced by the antagonism of apomorphine in dogs. It lowers the incidence of nausea and vomiting during surgical procedures and provides antiemetic protection in the postoperative period.

Droperidol potentiates other CNS depressants. It produces mild alpha-adrenergic blockade, peripheral vascular dilatation and reduction of the pressor effect of epinephrine. It can produce hypotension and decreased peripheral vascular resistance and may decrease pulmonary arterial pressure (particularly if it is abnormally high). It may reduce the incidence of epinephrine-induced arrhythmias but it does not prevent other cardiac arrhythmias.

The onset of action of single intramuscular and intravenous doses is from three to ten minutes following administration, although the peak effect may not be apparent for up to thirty minutes. The duration of the tranquilizing and sedative effects generally is two to four hours, although alteration of alertness may persist for as long as twelve hours.

INDICATIONS AND USAGE

Droperidol Injection is indicated to reduce the incidence of nausea and vomiting associated with surgical and diagnostic procedures.

CONTRAINDICATIONS

Droperidol is contraindicated in patients with known or suspected QT prolongation (i.e., QTc interval greater than 440 msec for males or 450 msec for females). This would include patients with congenital long QT syndrome.

Droperidol is contraindicated in patients with known hypersensitivity to the drug.

Droperidol is not recommended for any use other than for the treatment of perioperative nausea and vomiting in patients for whom other treatments are ineffective or inappropriate (see WARNINGS).

WARNINGS

Droperidol should be administered with extreme caution in the presence of risk factors for development of prolonged QT syndrome, such as: 1) clinically significant bradycardia (less than 50 bpm), 2) any clinically significant cardiac disease, 3) treatment with Class I and Class III antiarrhythmics, 4) treatment with monoamine oxidase inhibitors (MAOI's), 5) concomitant treatment with other drug products known to prolong the QT interval (see PRECAUTIONS, Drug Interactions), and 6) electrolyte imbalance, in particular hypokalemia and hypomagnesemia, or concomitant treatment with drugs (e.g., diuretics) that may cause electrolyte imbalance.

Effects on Cardiac Conduction:

A dose-dependent prolongation of the QT interval was observed within 10 minutes of droperidol administration in a study of 40 patients without known cardiac disease who underwent extracranial head and neck surgery. Significant QT prolongation was observed at all three dose levels evaluated, with 0.1, 0.175, and 0.25 mg/kg associated with prolongation of median QTc by 37,44, and 59 msec, respectively.

Cases of QT prolongation and serious arrhythmias (e.g., torsade de pointes, ventricular arrhythmias, cardiac arrest, and death) have been observed during post-marketing treatment with droperidol. Some cases have occurred in patients with no known risk factors and at doses at or below recommended doses. There has been at least one case of nonfatal torsade de pointes confirmed by rechallenge.

Based on these reports, all patients should undergo a 12-lead ECG prior to administration of droperidol to determine if a prolonged QT interval (i.e., QTc greater than 440 msec for males or 450 msec for females) is present. If there is a prolonged QT interval, droperidol should NOT be administered. For patients in whom the potential benefit of droperidol treatment is felt to outweigh the risks of potentially serious arrhythmias, ECG monitoring should be performed prior to treatment and continued for 2-3 hours after completing treatment to monitor for arrhythmias.

FLUIDS AND OTHER COUNTERMEASURES TO MANAGE HYPOTENSION SHOULD BE READILY AVAILABLE.

As with other CNS depressant drugs, patients who have received droperidol should have appropriate surveillance.

It is recommended that opioids, when required, initially be used in reduced doses.

As with other neuroleptic agents, very rare reports of neuroleptic malignant syndrome (altered consciousness, muscle rigidity and autonomic instability) have occurred in patients who have received droperidol.

Since it may be difficult to distinguish neuroleptic malignant syndrome from malignant hyperpyrexia in the perioperative period, prompt treatment with dantrolene should be considered if increases in temperature, heart rate or carbon dioxide production occur.

PRECAUTIONS

General

The initial dose of droperidol should be appropriately reduced in elderly, debilitated and other poor-risk patients. The effect of the initial dose should be considered in determining incremental doses.

Certain forms of conduction anesthesia, such as spinal anesthesia and some peridural anesthetics, can alter respiration by blocking intercostal nerves and can cause peripheral vasodilation and hypotension because of sympathetic blockade. Through other mechanisms (see CLINICAL PHARMACOLOGY), droperidol can also alter circulation. Therefore, when droperidol is used to supplement these forms of anesthesia, the anesthetist should be familiar with the physiological alterations involved, and be prepared to manage them in the patients elected for these forms of anesthesia.

If hypotension occurs, the possibility of hypovolemia should be considered and managed with appropriate parenteral fluid therapy. Repositioning the patient to improve venous return to the heart should be considered when operative conditions permit. It should be noted that in spinal and peridural anesthesia, tilting the patient into a head-down position may result in a higher level of anesthesia than is desirable, as well as impair venous return to the heart. Care should be exercised in moving and positioning of patients because of a possibility of orthostatic hypotension. If volume expansion with fluids plus these other countermeasures do not correct the hypotension, then the administration of pressor agents other than epinephrine should be considered. Epinephrine may paradoxically decrease the blood pressure in patients treated with droperidol due to the alpha-adrenergic blocking action of droperidol.

Since droperidol may decrease pulmonary arterial pressure, this fact should be considered by those who conduct diagnostic or surgical procedures where interpretation of pulmonary arterial pressure measurements might determine final management of the patient.

Vital signs and ECG should be monitored routinely.

When the EEG is used for postoperative monitoring, it may be found that the EEG pattern returns to normal slowly.

Impaired Hepatic or Renal Function:

Droperidol should be administered with caution to patients with liver and kidney dysfunction because of the importance of these organs in the metabolism and excretion of drugs.

Pheochromocytoma:

In patients with diagnosed/suspected pheochromocytoma, severe hypertension and tachycardia have been observed after the administration of droperidol.

Drug Interactions

Potentially Arrhythmogenic Agents:

Any drug known to have the potential to prolong the QT interval should not be used together with droperidol. Possible pharmacodynamic interactions can occur between droperidol and potentially arrhythmogenic agents such as class I or III antiarrhythmics, antihistamines that prolong the QT interval, antimalarials, calcium channel blockers, neuroleptics that prolong the QT interval, and antidepressants.

Caution should be used when patients are taking concomitant drugs known to induce hypokalemia or hypomagnesemia as they may precipitate QT prolongation and interact with droperidol. These would include diuretics, laxatives and supraphysiological use of steroid hormones with mineralocorticoid potential.

CNS Depressant Drugs:

Other CNS depressant drugs (e.g. barbiturates, tranquilizers, opioids and general anesthetics) have additive or potentiating effects with droperidol. When patients have received such drugs, the dose of droperidol required will be less than usual. Following the administration of droperidol, the dose of other CNS depressant drugs should be reduced.

Carcinogenesis, Mutagenesis, Impairment of Fertility

No carcinogenicity studies have been carried out with droperidol. The micronucleus test in female rats revealed no mutagenic effects in single oral doses as high as 160 mg/kg. An oral study in rats (Segment 1) revealed no impairment of fertility in either males or females at 0.63, 2.5 and 10 mg/kg doses (approximately 2, 9 and 36 times maximum recommended human iv/im dosage).

Pregnancy

Category C. Droperidol administered intravenously has been shown to cause a slight increase in mortality of the newborn rat at 4.4 times the upper human dose. At 44 times the upper human dose, mortality rate was comparable to that for control animals. Following intramuscular administration, increased mortality of the offspring at 1.8 times the upper human dose is attributed to CNS depression in the dams who neglected to remove placentae from their offspring. Droperidol has not been shown to be teratogenic in animals. There are no adequate and well-controlled studies in pregnant women. Droperidol should be used during pregnancy only if the potential benefit justifies the potential risk to the fetus.

Labor and Delivery

There are insufficient data to support the use of droperidol in labor and delivery. Therefore, such use is not recommended.

Nursing Mothers

It is not known whether droperidol is excreted in human milk. Because many drugs are excreted in human milk, caution should be exercised when droperidol is administered to a nursing mother.

Pediatric Use

The safety of droperidol in children younger than two years of age has not been established.

ADVERSE REACTIONS

QT interval prolongation, torsade de pointes, cardiac arrest, and ventricular tachycardia have been reported in patients treated with droperidol. Some of these cases were associated with death. Some cases occurred in patients with no known risk factors, and some were associated with droperidol doses at or below recommended doses.

Physicians should be alert to palpitations, syncope, or other symptoms suggestive of episodes of irregular cardiac rhythm in patients taking droperidol and promptly evaluate such cases (see WARNINGS, Effects on Cardiac Conduction).

The most common somatic adverse reactions reported to occur with droperidol are mild to moderate hypotension and tachycardia, but these effects usually subside without treatment. If hypotension occurs and is severe or persists, the possibility of hypovolemia should be considered and managed with appropriate parenteral fluid therapy.

The most common behavioral adverse effects of droperidol include dysphoria, postoperative drowsiness, restlessness, hyperactivity and anxiety, which can either be the result of an inadequate dosage (lack of adequate treatment effect) or of an adverse drug reaction (part of the symptom complex of akathisia).

Care should be taken to search for extrapyramidal signs and symptoms (dystonia, akathisia, oculogyric crisis) to differentiate these different clinical conditions. When extrapyramidal symptoms are the cause, they can usually be controlled with anticholinergic agents.

Postoperative hallucinatory episodes (sometimes associated with transient periods of mental depression) have also been reported.

Other less common reported adverse reactions include anaphylaxis, dizziness, chills and/or shivering, laryngospasm and bronchospasm.

Elevated blood pressure, with or without pre-existing hypertension, has been reported following administration of droperidol combined with fentanyl citrate or other parenteral analgesics. This might be due to unexplained alterations in sympathetic activity following large doses; however, it is also frequently attributed to anesthetic or surgical stimulation during light anesthesia.

OVERDOSAGE

Manifestations:

The manifestations of droperidol overdosage are an extension of its pharmacologic actions and may include QT prolongation and serious arrhythmias (e.g., torsade de pointes) (see BOXED WARNING, WARNINGS, and PRECAUTIONS).

Treatment:

In the presence of hypoventilation or apnea, oxygen should be administered and respiration should be assisted or controlled as indicated. A patent airway must be maintained; an oropharyngeal airway or endotracheal tube might be indicated. The patient should be carefully observed for 24 hours; body warmth and adequate fluid intake should be maintained. If hypotension occurs and is severe or persists, the possibility of hypovolemia should be considered and managed with appropriate parenteral fluid therapy. (see PRECAUTIONS).

If significant extrapyramidal reactions occur in the context of an overdose, an anticholinergic should be administered.

The intravenous Median Lethal Dose of droperidol is 20-43 mg/kg in mice; 30 mg/kg in rats; 25 mg/kg in dogs and 11-13 mg/kg in rabbits. The intramuscular Median Lethal Dose of droperidol is 195 mg/kg in mice; 104-110 mg/kg in rats; 97 mg/kg in rabbits and 200 mg/kg in guinea pigs.

DOSAGE AND ADMINISTRATION

Dosage should be individualized. Some of the factors to be considered in determining the dose are age, body weight, physical status, underlying pathological condition, use of other drugs, type of anesthesia to be used, and the surgical procedure involved.

Vital signs and ECG should be monitored routinely.

Adult Dosage: The maximum recommended initial dose of droperidol is 2.5 mg IM or slow IV. Additional 1.25 mg doses of droperidol may be administered to achieve the desired effect. However, additional doses should be administered with caution, and only if the potential benefit outweighs the potential risk.

Children’s Dosage: For children two to 12 years of age, the maximum recommended initial dose is 0.1 mg/kg, taking into account the patient's age and other clinical factors. However, additional doses should be administered with caution, and only if the potential benefit outweighs the potential risk.

See WARNINGS and PRECAUTIONS for use of droperidol with other CNS depressants, and in patients with altered response.

Parenteral drug products should be inspected visually for particulate matter and discoloration prior to administration, whenever solution and container permit. If such abnormalities are observed, the drug should not be administered.

HOW SUPPLIED

Droperidol Injection USP, (2.5 mg/mL) is available as:

Product No. | Strength | Size | How Packaged
NDC 0517-9702-25 | 5 mg/2 mL | 2 mL Single Dose Vial | Boxes of 25

Store at 20° to 25°C (68° to 77°F); excursions permitted to 15° to 30°C (59° to 86°F) (See USP Controlled Room Temperature).

PROTECT FROM LIGHT. RETAIN IN CARTON UNTIL TIME OF USE.

REFERENCES

1. Saarnivaara L, Klemola UM, Lindgren L, et al. QT interval of the ECG, heart rate and arterial pressure using propofol, methohexital or midazolam for induction of anaesthesia. Acta Anaesthesiol Scand 1990: 34: 276-81.
2. Schmeling WT, Warltier DC, McDonald DJ, et al. Prolongation of the QT interval by enflurane, isoflurane and halothane in humans. Anesth Analg 1991:72:137-44.
3. Spath G. Torsade des pointe oder die andere Ursache des plotz-lichen Herztodes. Wien: Ueberreuter. 1998.
4. Riley DC, Schmeling WT, al-Wathiqui MH, et al. Prolongation of the QT interval by volatile anesthetics in chronically instrumented dogs. Anesth Analg 1988: 67:741-9.
5. McConachie I, Keaveny JP, Healy TE, et al. Effects of anaesthesia on the QT interval. Br J Anaesth 1989:63:558-60.
6. Lawrence KR, Nasraway SA. Conduction disturbances associated with administration of butyrophenone antipsychotics in the critically ill: a review of the literature. Pharmacother 1997: 17(3):531-7.
7. Lischke V, Behne M, Doelken P, et al. Droperidol causes a dose-dependent prolongation of the QT interval. Anesth Analg 1994:79:983-6.

AMERICAN
REGENT, INC.
SHIRLEY, NY 11967

IN9702
Rev. 1/09

PACKAGE LABEL.PRINICIPAL DISPLAY PANEL - Container

NDC 0517-9702-01
Rx Only
Droperidol Injection, USP

5 mg/2 mL (2.5 mg/mL)

For Intravenous or Intramuscular Use
2 mL Single-Dose Vial
Discard Unused Portion

PACKAGE LABEL.PRINCIPAL DISPLAY PANEL - Carton

NDC 0517-9702-25

DROPERIDOL INJECTION, USP

5 mg/2 mL (2.5 mg/mL)

For Intravenous or Intramuscular Use

25 X 2 mL Single-Dose Vials
Discard Unused Portion

AMERICAN REGENT, INC.
SHIRLEY, NY 11967